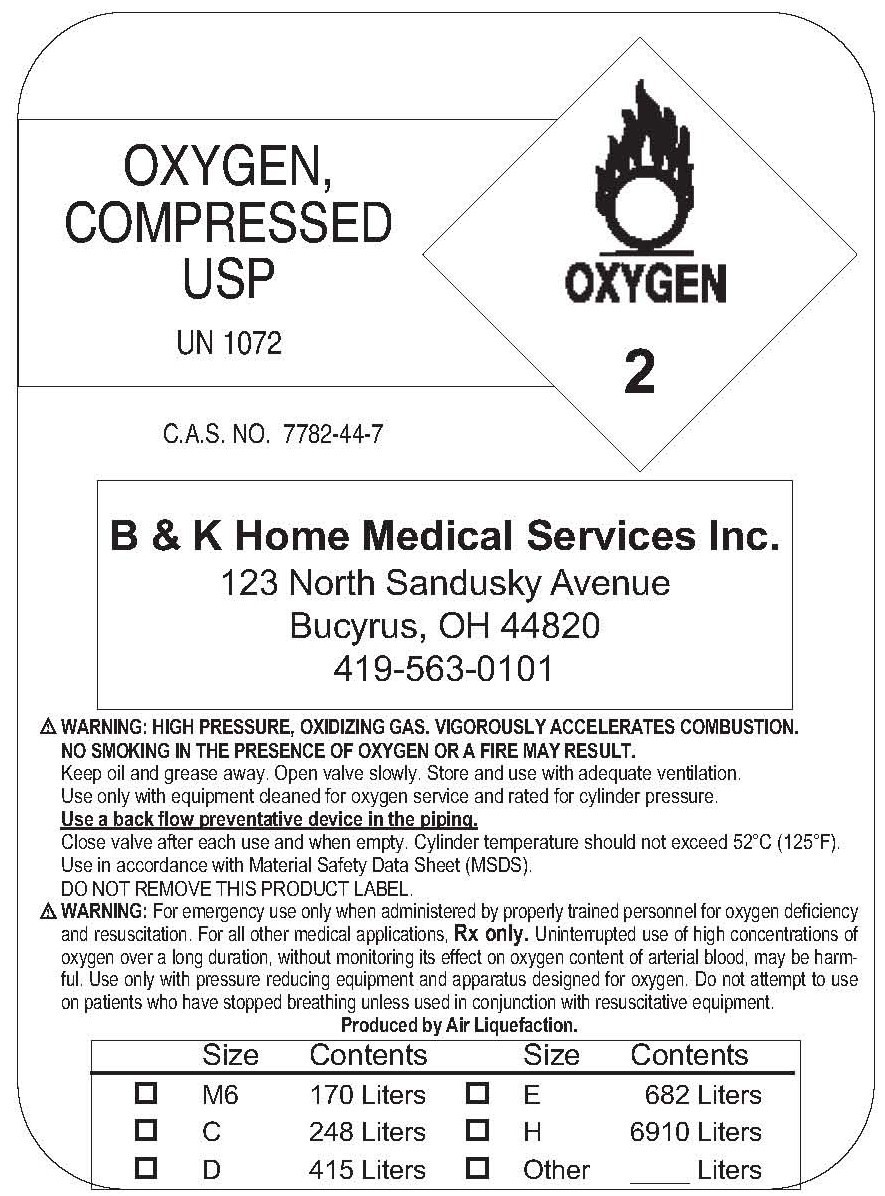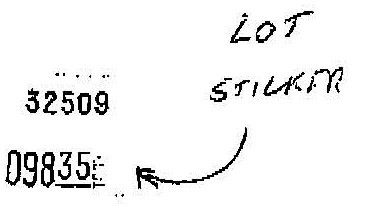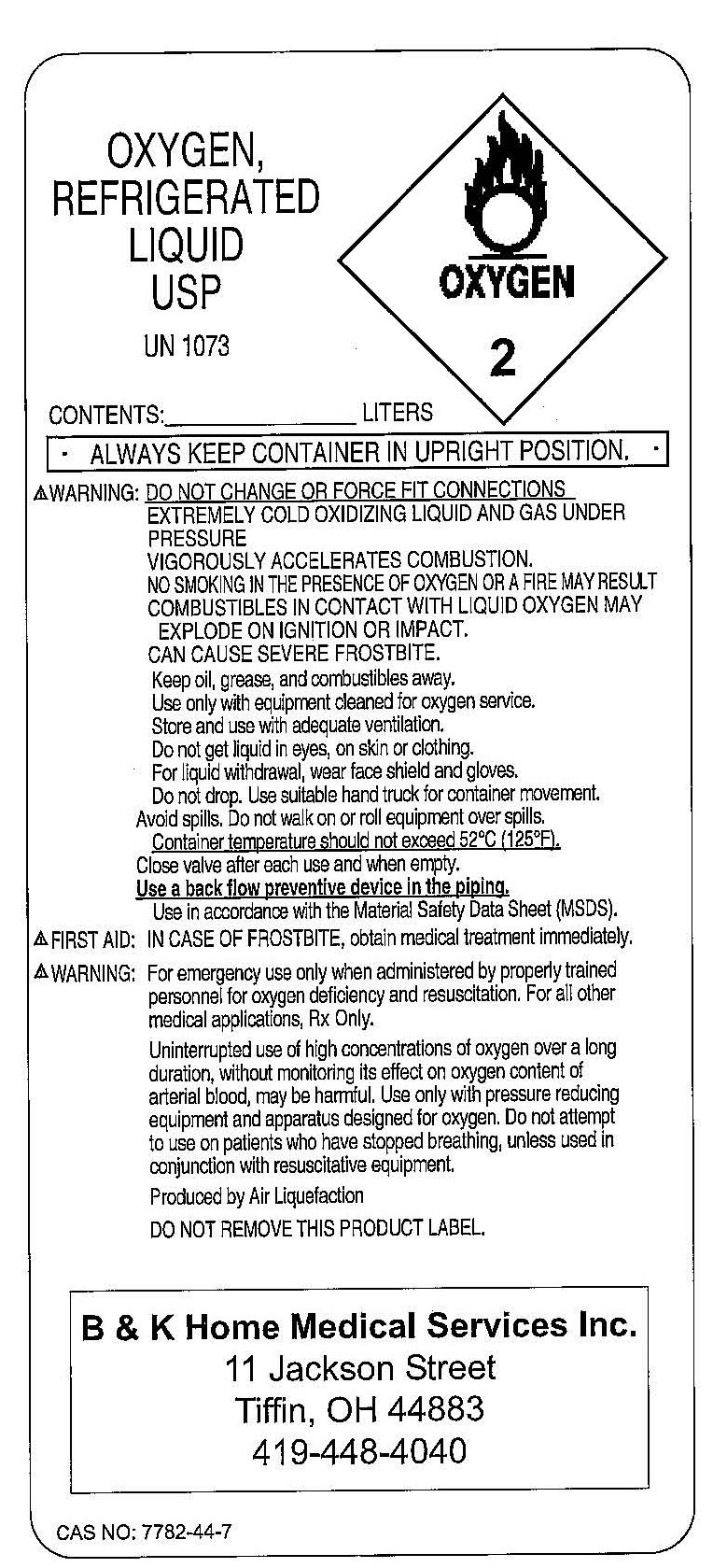 DRUG LABEL: Oxygen
NDC: 54300-0001 | Form: GAS
Manufacturer: B&K Home Medical Services, Inc. 
Category: prescription | Type: HUMAN PRESCRIPTION DRUG LABEL
Date: 20090924

ACTIVE INGREDIENTS: Oxygen 99 L/100 L

Oxygen